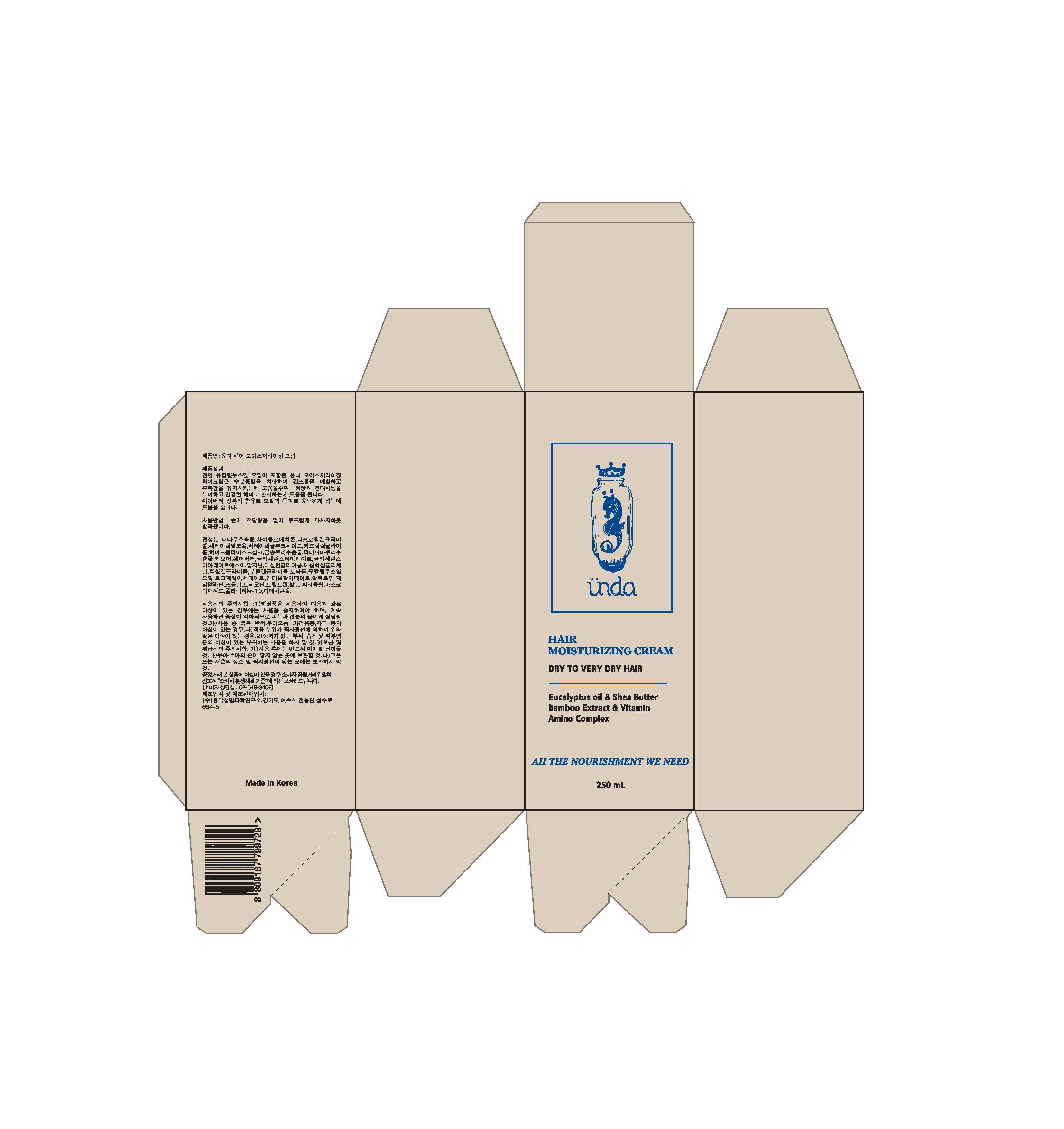 DRUG LABEL: UNDA HAIR MOISTURIZING
NDC: 70845-0010 | Form: CREAM
Manufacturer: UNDA
Category: otc | Type: HUMAN OTC DRUG LABEL
Date: 20160724

ACTIVE INGREDIENTS: EUCALYPTUS GLOBULUS LEAF 0.05 g/100 mL; BAMBUSA VULGARIS TOP 52.51 g/100 mL; SHEA BUTTER 1 g/100 mL
INACTIVE INGREDIENTS: DIPROPYLENE GLYCOL; ALLANTOIN

Drug Facts

ACTIVE INGREDIENT

Bambusa Vulgaris Extract, Butyrospermum Parkii (Shea) Butter, Eucalyptus Globulus Leaf Oil

INACTIVE INGREDIENT

Cyclomethicone, Dipropylene Glycol, Cetearyl Alcohol, Cetearyl Glucoside, Caprylyl Glycol, Hydrolyzed Silk, Sciadopitys Verticillata Root Extract, Krameria Triandra Root Extract, Carbomer, Glyceryl Stearat, Glyceryl Stearate SE, Arginine, Decylene Glycol. Ethylhexylglycerin, Hexylene Glycol, Butylene Glycol, Totarol, Tocopheryl Acetate, Retinyl Palmitate, Allantoin, Phenylalanine, Proline, Threonine, Tryptophan, Valine, Pyridoxine, Ascorbic Acid, Polyquaternium-10, Dimethiconol

PURPOSE

Helps alleviate the concerns such as hair loss, dandruff, and dryness.

keep out of reach of the children

INDICATIONS AND USAGE

1. Wet your hair with plenty of lukewarm water.
2. Use two pumps of Unda moisturizing shampoo (depending on hair length and amount of hair, three pumps may be applicable)
3. Use your fingertips to rub your scalp and make plenty of bubbles.
4. Enjoy its natural scent and massage lightly for 2~3minutes.
5. Wash off with lukewarm water.
6. Dry with dry towel.
7. Use one pump of Unda moisturizing cream to apply directly on your hair thoroughly.
8. Hair Dry

WARNINGS

1. Do not use in the following cases(Eczema and scalp wounds)
2.Side Effects
1)Due to the use of this product if rash, irritation, itching and symptopms of hypersnesitivity occur, dicontinue use and consult your phamacisr or doctor
3.General Precautions
1)If in contact with the eyes, wash out thoroughty with water If the symptoms are servere, seek medical advice immediately
2)This product is for exeternal use only. Do not use for internal use
4.Storage and handling precautions
1)If possible, avoid direct sunlight and store in cool and area of low humidity
2)In order to maintain the quality of the product and avoid misuse
3)Avoid placing the product near fire and store out in reach of children

DOSAGE AND ADMINISTRATION

for external use only